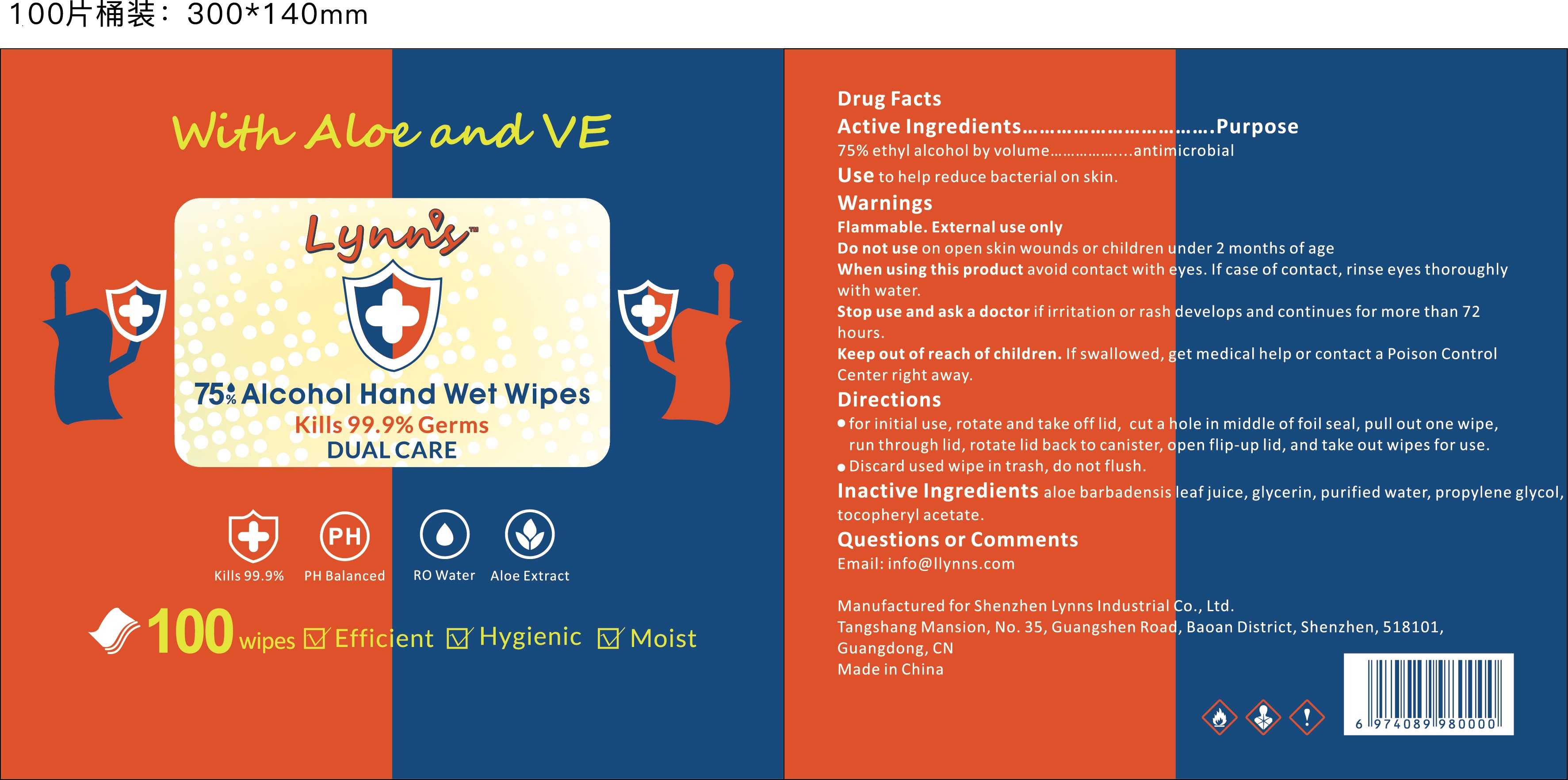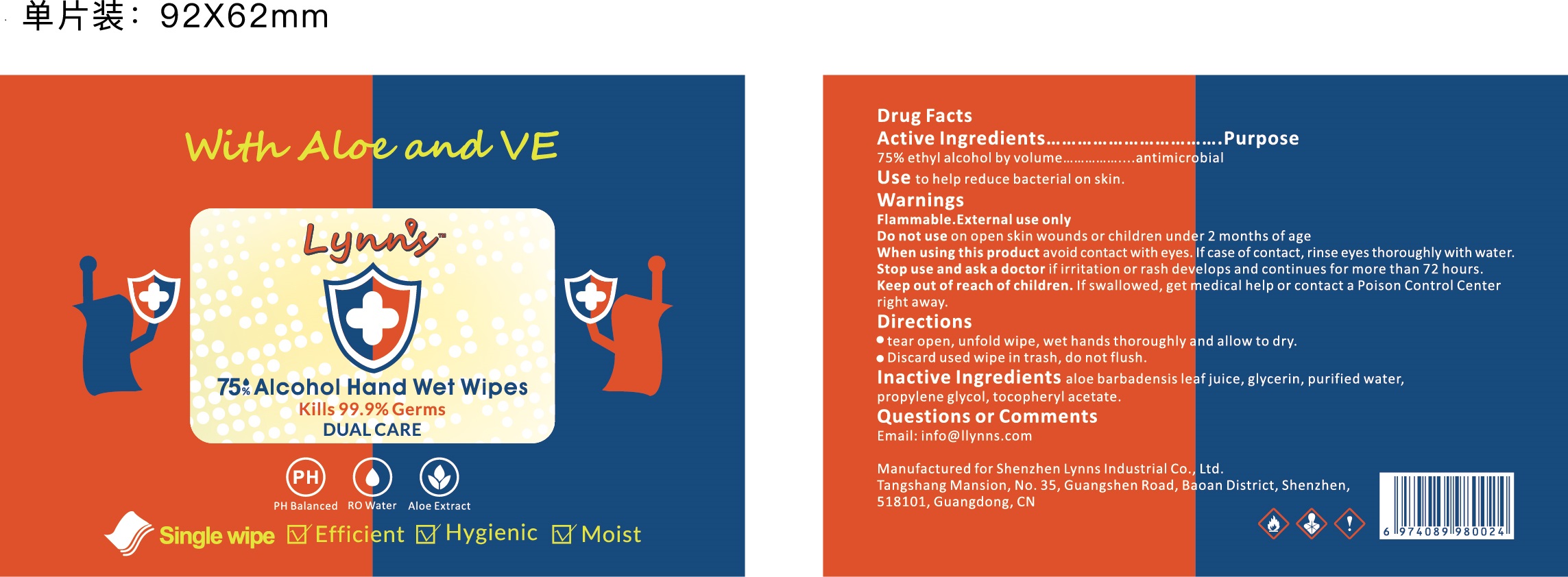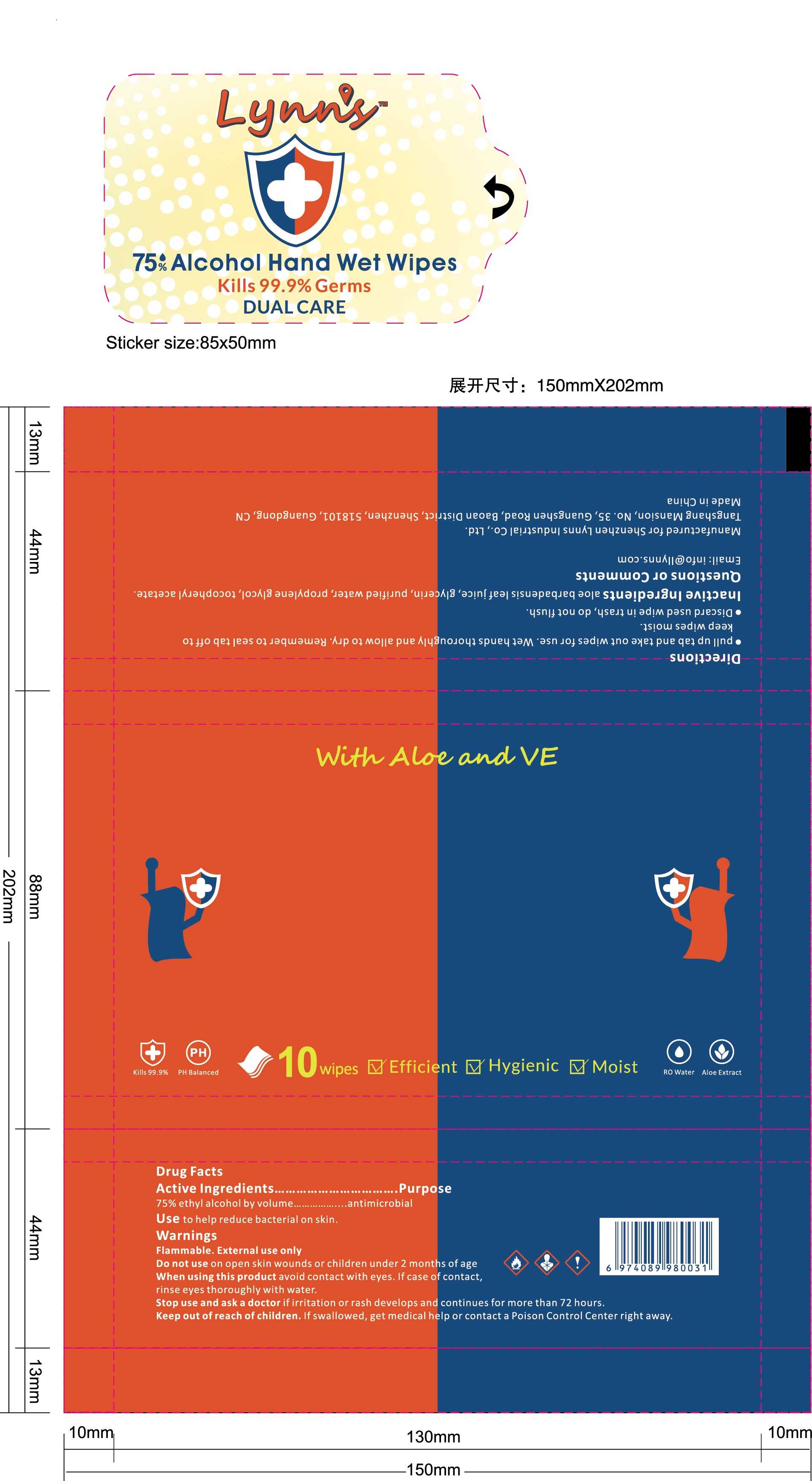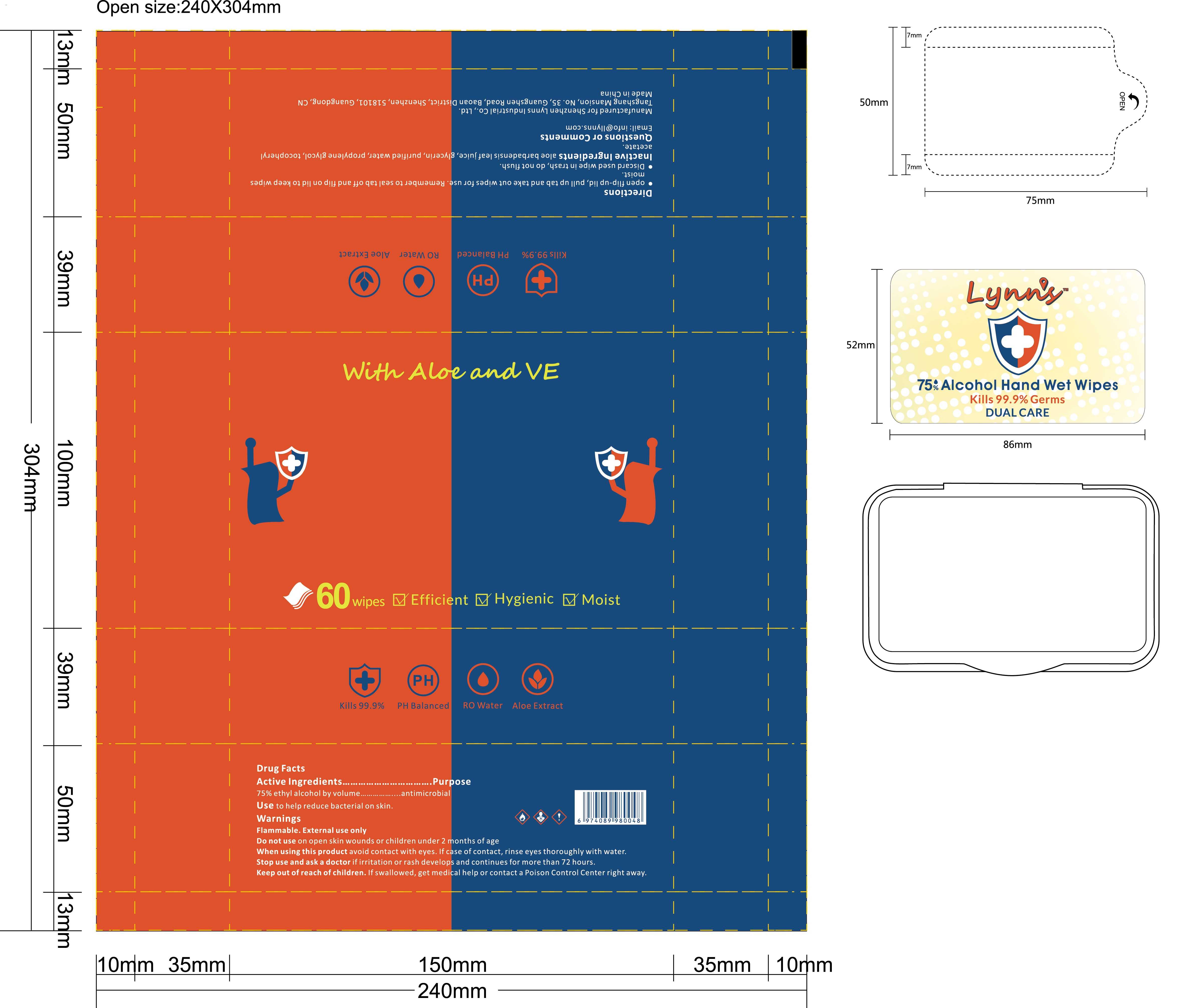 DRUG LABEL: 75% Alcohol Wet Wipes
NDC: 81422-001 | Form: CLOTH
Manufacturer: Shenzhen Lynns Industrial Co., Ltd.
Category: otc | Type: HUMAN OTC DRUG LABEL
Date: 20210118

ACTIVE INGREDIENTS: ALCOHOL 75 mL/100 1
INACTIVE INGREDIENTS: GLYCERIN; ALOE VERA LEAF; WATER; PROPYLENE GLYCOL; ALPHA-TOCOPHEROL ACETATE

81422-001
75% Alcohol Wet Wipes

Active Ingredient(s)

75%ethyl alcohol by volume....antimicrobial

Purpose

antimicrobial

Use

Use to help reduce bacterial on skin.

Warnings

Flammable.External use only

Do not use on open skin wounds or children under 2 months of age

When using this product avoid contact with eyes.If case of contact, rinse eyes thoroughly with water.

Stop use and ask a doctor if irritation or rash develops and continues for more than 72 hours.

Keep out of reach of children.If swallowed, get medical help or contact a Poison Control Center right away.

Do not use on open skin wounds or children under 2 months of age

When using this product avoid contact with eyes.If case of contact, rinse eyes thoroughly with water.

Stop use and ask a doctor if irritation or rash develops and continues for more than 72 hours.

Keep out of reach of children.If swallowed, get medical help or contact a Poison Control Center right away.

Stop use and ask a doctor if irritation or rash develops and continues for more than 72 hours.

Keep out of reach of children.If swallowed, get medical help or contact a Poison Control Center right away.

Directions

·for initial use, rotate and take off lid, cut a hole in middle of foil seal, pull out one wipe, run through lid, rotate lid back to canister, open flip-up lid, and take out wipes for use.
·Discard used wipe in trash, do not flush.

Other information

- Store between 15-30C (59-86F)
- Avoid freezing and excessive heat above 40C (104F)

Inactive ingredients

aloe barbadensis leaf juice, glycerin, purified water, propylene glycol, tocopheryl acetate.

glycerin, hydrogen peroxide, purified water USP

Package Label - Principal Display Panel

81422-001-00--Alcohol Wet Wipes 100wipes

81422-001-01--Alcohol Wet Wipes 1 wipe

81422-001-10--Alcohol Wet Wipes 10wipes

81422-001-60--Alcohol Wet Wipes 60wipes